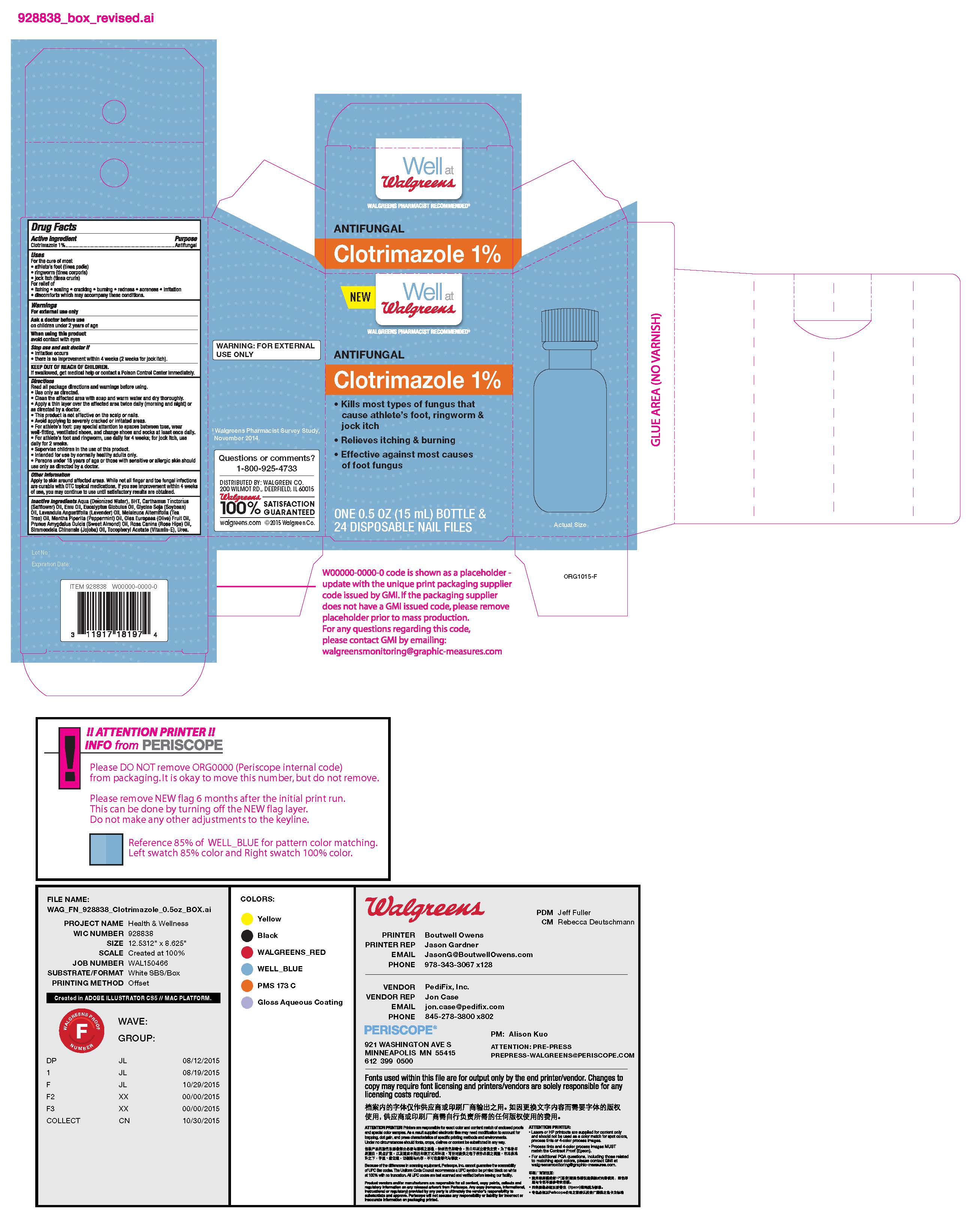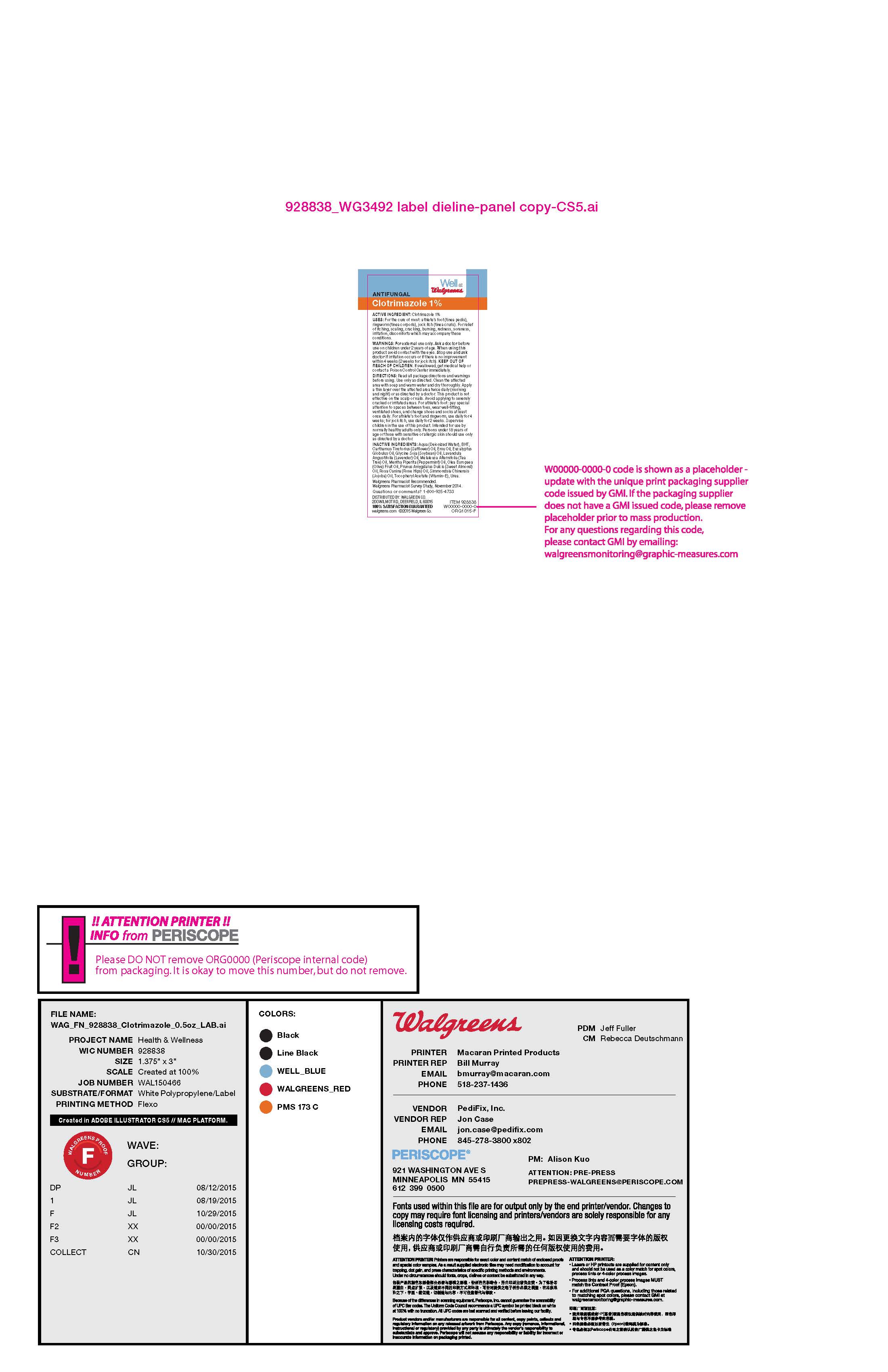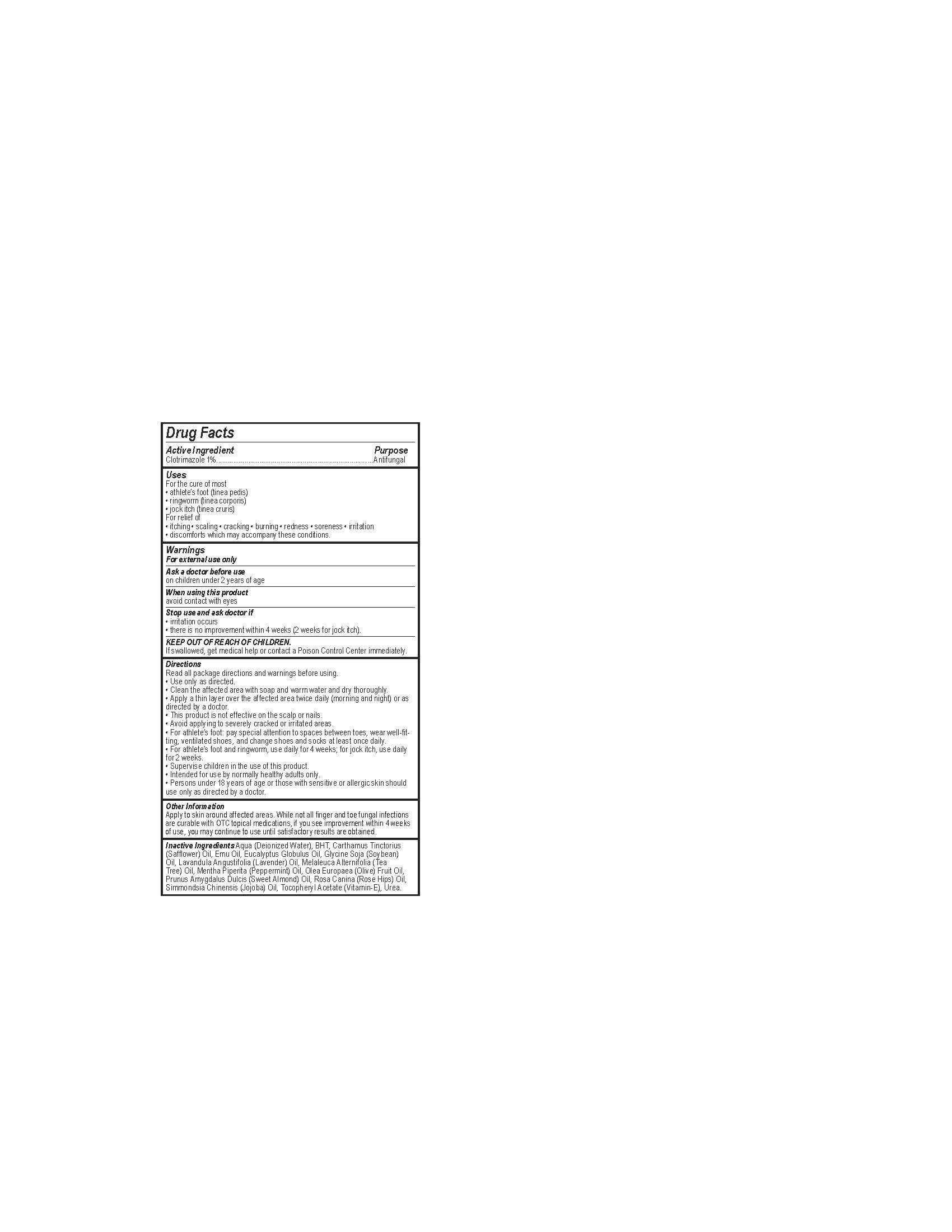 DRUG LABEL: Clotrimazole
NDC: 0363-3492 | Form: LIQUID
Manufacturer: Walgreens
Category: otc | Type: HUMAN OTC DRUG LABEL
Date: 20191102

ACTIVE INGREDIENTS: CLOTRIMAZOLE 1 mg/1 mL
INACTIVE INGREDIENTS: CARTHAMUS TINCTORIUS FLOWER OIL; MENTHA PIPERITA; SIMMONDSIA CHINENSIS WHOLE; EMU OIL; OLEA EUROPAEA FRUIT VOLATILE OIL; ALMOND OIL; UREA; EUCALYPTUS GLOBULUS WHOLE; ROSA CANINA FLOWER OIL; WATER; BUTYLATED HYDROXYTOLUENE; LAVENDER OIL; MELALEUCA ALTERNIFOLIA WHOLE; SOYBEAN OIL; .ALPHA.-TOCOPHEROL SUCCINATE, D-

Clotrimazole

ACTIVE INGREDIENT

clotrimazole 1%

WARNINGS

For external use only

Ask a doctor before use on children under 2 years of age

When using this product avoid contact with eyes

Stop use and ask doctor if: irritation occurs, there is no improvement within 4 weeks (2 weeks for jock itch)

PURPOSE

Antifungal

DOSAGE AND ADMINISTRATION

• Use only as directed.

• Clean the affected area with soap and warm water and dry thoroughly.

• Apply a thin layer over the affected area twice daily (morning and night) or as directed by a doctor.

• This product is not effective on the scalp or nails.

• Avoid applying to severely cracked or irritated areas.

• For athlete’s foot: pay special attention to spaces between toes, wear well-fit- ting, ventilated shoes, and change shoes and socks at least once daily.

• For athlete’s foot and ringworm, use daily for 4 weeks; for jock itch, use daily

for 2 weeks.

• Super vise children in the use of this product.

• Intended for use by normally healthy adults only.

• Persons under 18 years of age or those with sensitive or allergic skin should use only as directed by a doctor.

KEEP OUT OF REACH OF CHILDREN.

If swallowed, get medical help or contact a Poison Control Center immediately.

INACTIVE INGREDIENT

Aqua (Deionized Water), BHT, Car thamus Tinctorius (Saf flower) Oil, Emu Oil, Eucalyptus Globulus Oil, Glycine Soja (Soybean) Oil, Lavandula Angustifolia (Lavender) Oil, Melaleuca Alternifolia (Tea

Tree) Oil, Mentha Piperita (Peppermint) Oil, Olea Europaea (Olive) Fruit Oil, Prunus Amygdalus Dulcis (Sweet Almond) Oil, Rosa Canina (Rose Hips) Oil, Simmondsia Chinensis (Jojoba) Oil, Tocopher yl Acetate (Vitamin- E), Urea.

INDICATIONS AND USAGE

For the cure of most

• athlete’s foot (tinea pedis)

• ringworm (tinea corporis)

• jock itch (tinea cruris) For relief of

• itching • scaling • cracking • burning • redness • soreness • irritation

• discomforts which may accompany these conditions.